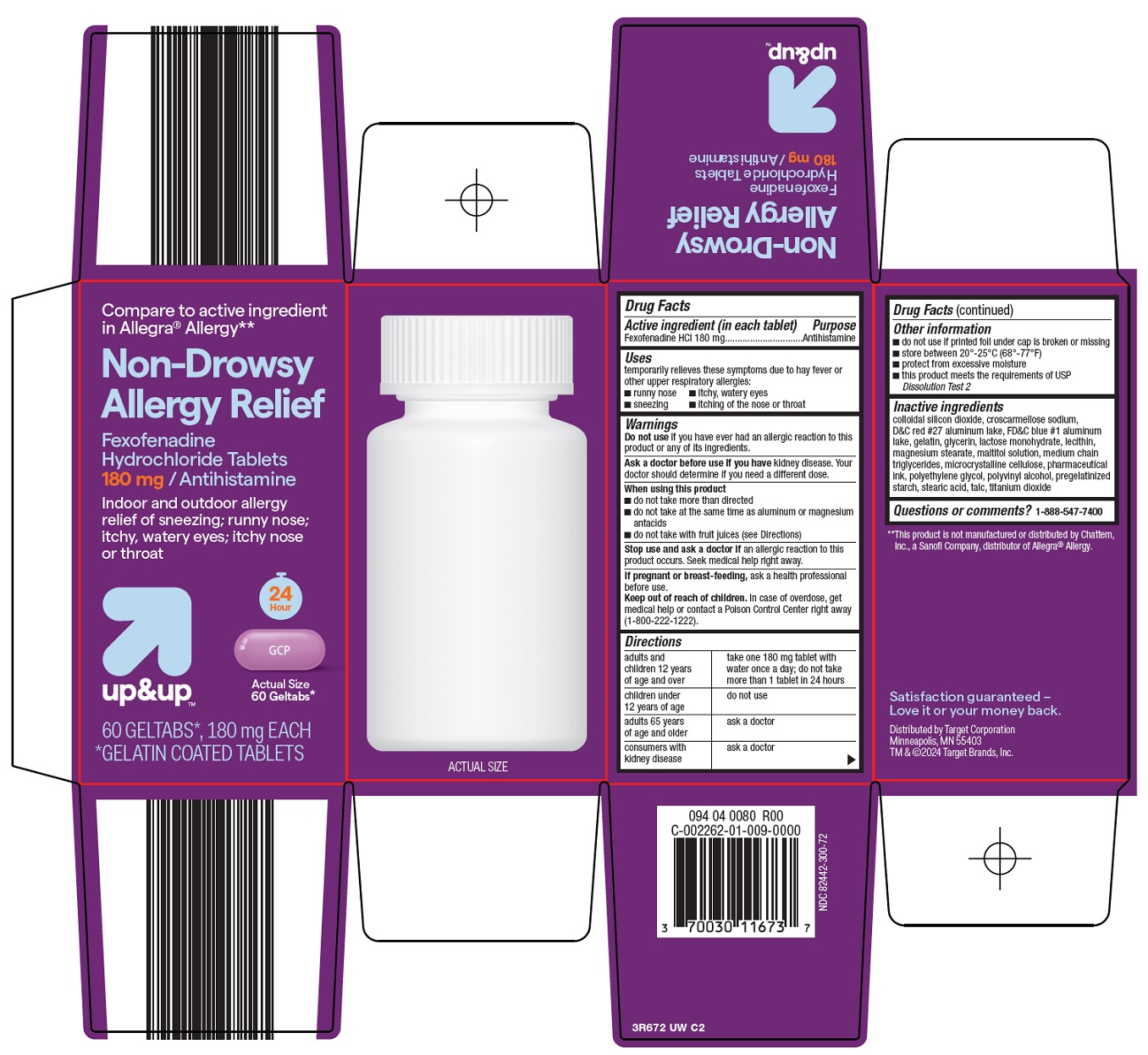 DRUG LABEL: up and up non drowsy allergy relief
NDC: 82442-300 | Form: TABLET, COATED
Manufacturer: Target Corporation
Category: otc | Type: HUMAN OTC DRUG LABEL
Date: 20250819

ACTIVE INGREDIENTS: FEXOFENADINE HYDROCHLORIDE 180 mg/1 1
INACTIVE INGREDIENTS: SILICON DIOXIDE; CROSCARMELLOSE SODIUM; D&C RED NO. 27 ALUMINUM LAKE; FD&C BLUE NO. 1 ALUMINUM LAKE; GELATIN, UNSPECIFIED; GLYCERIN; LACTOSE MONOHYDRATE; MAGNESIUM STEARATE; MALTITOL; MEDIUM-CHAIN TRIGLYCERIDES; MICROCRYSTALLINE CELLULOSE; POLYETHYLENE GLYCOL, UNSPECIFIED; POLYVINYL ALCOHOL, UNSPECIFIED; STEARIC ACID; TALC; TITANIUM DIOXIDE

Target Corporation Non-Drowsy Allergy Relief Drug Facts

Active ingredient (in each tablet)

Fexofenadine HCl 180 mg

Purpose

Antihistamine

Uses

temporarily relieves these symptoms due to hay fever or other upper respiratory allergies:

- runny nose
- itchy, watery eyes
- sneezing
- itching of the nose or throat

Warnings

Do not use

if you have ever had an allergic reaction to this product or any of its ingredients.

Ask a doctor before use if you have

kidney disease. Your doctor should determine if you need a different dose.

When using this product

- do not take more than directed
- do not take at the same time as aluminum or magnesium antacids
- do not take with fruit juices (see Directions)

Stop use and ask a doctor if

an allergic reaction to this product occurs. Seek medical help right away.

If pregnant or breast-feeding,

ask a health professional before use.

Keep out of reach of children.

In case of overdose, get medical help or contact a Poison Control Center right away (1-800-222-1222).

Directions

adults and children 12 years of age and over | take one 180 mg tablet with water once a day; do not take more than 1 tablet in 24 hours
children under 12 years of age | do not use
adults 65 years of age and older | ask a doctor
consumers with kidney disease | ask a doctor

Other information

- do not use if printed foil under cap is broken or missing
- store between 20°-25°C (68°-77°F)
- protect from excessive moisture
- this product meets the requirements of USP Dissolution Test 2

Inactive ingredients

colloidal silicone dioxide, croscarmellose sodium, D&C red #27 aluminum lake, FD&C blue #1 aluminum lake, gelatin, glycerin, lactose monohydrate, lecithin, magnesium stearate, maltitol solution, medium chain triglycerides, microcrystalline cellulose, pharmaceutical ink, polyethylene glycol, polyvinyl alcohol, pregelatinized starch, stearic acid, talc, titanium dioxide

Questions or comments?

1-888-547-7400

Package/Label Principal Display Panel

Compare to active ingredient in Allegra® Allergy

Non-Drowsy Allergy Relief

Fexofenadine Hydrochloride Tablets 180 mg / Antihistamine

Indoor and outdoor allergy relief of sneezing; runny nose; itchy, watery eyes; itchy nose or throat

24 Hour

up&up™

Actual Size

60 Geltabs*

60 GELTABS*, 180 mg EACH

*GELATIN COATED TABLETS